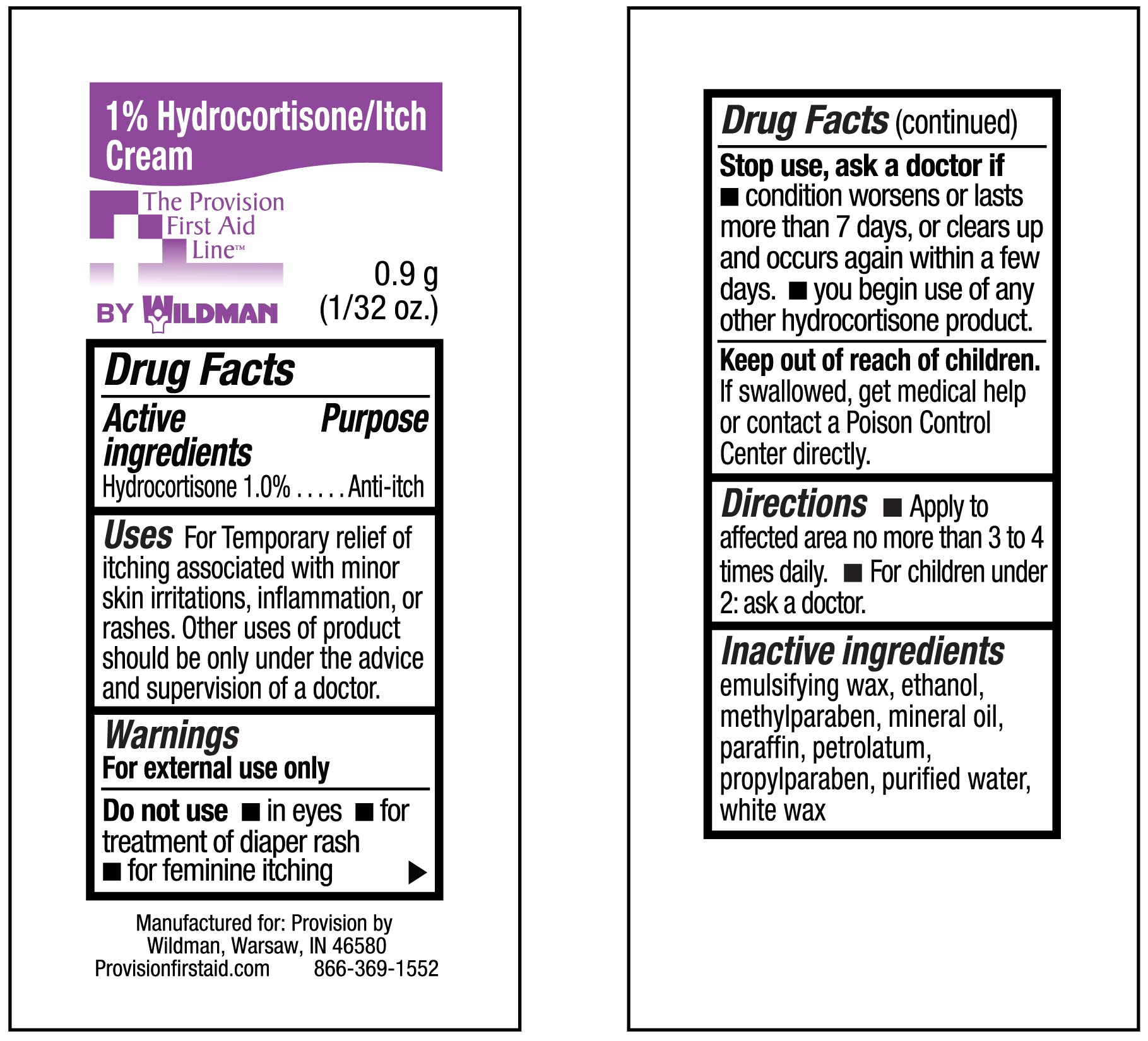 DRUG LABEL: Itch and Rash Cream
NDC: 84269-4506 | Form: CREAM
Manufacturer: Wildman Business Group
Category: otc | Type: HUMAN OTC DRUG LABEL
Date: 20240901

ACTIVE INGREDIENTS: HYDROCORTISONE 10 mg/1 g
INACTIVE INGREDIENTS: ANHYDROUS CITRIC ACID; GLYCERIN; GLYCERYL MONOSTEARATE; METHYLPARABEN; PETROLATUM; POLYSORBATE 80; PROPYLPARABEN; PROPYLENE GLYCOL; WATER; ANHYDROUS TRISODIUM CITRATE; TITANIUM DIOXIDE

1% Hydrocortisone Itch Cream

Uses:

for the temporary relief of itching associated with minor skin irritations, inflammation and rashes due to eczema,

insect bites, poison ivy, poison oak, poison sumac, soaps, detergents, cosmetics, jewelry, seborrheic dermatitis, psoriasis and

scrapes

KEEP OUT OF REACH OF CHILDREN. iF SWALLOWED, get medical help or

contact a Poison Control Center right

away.

Warnings :

For external use only Do not use for the treatment of diaper rash

Consult a doctor:before use if you have a vaginal discharge (for external feminine itching):

for external itching, do not exceed the recommended daily dosage or if bleeding occurs

if condition worsens or if symptoms persist for more than 7 days or clear up and occur again within a few days

When using this product:avoid contact with eyes, do not put this product into rectum by using fingers or any mechanical

Do not use:with any other Hydrocortison product unless you have consulted a doctor

DOSAGE AND ADMINISTRATION

dIRECTIONS: fOR ADULTS AND CHILDREN 2 YEARS OF AGE AND OLDER-APPLY TO AFFECTED AREA NOT MORE THAN 3 OR 4 TIMES DAILY

CHILDREN UNDER 2 YEARS, DO NOT USE, CONSULT A DOCTOR. ADULTS FOR EXTERNAL ANAL ITCHING WHEN PRACTICAL-CLEANSE THE AFFECTED AREA WITH A MILD SOAP AND WARM WATER AND RINCE THOROUGHLY OR BY PATTING AND BLOTTING WITH AN APPROPRIATE CLEANSING PAD. GENTLY DRY BY PATTING OR BLOTTING WITH A SOFT CLOTH BEFORE APPLICATION OF THIS PRODUCT. CHILDREN UNDER 12 YEARS OF AGE-FOR EXTERNAL ANAL ITCHING, CONSULT A DOCTOR

INACTIVE INGREDIENT

INACTIVE INGREDIENTS:CITRIC acid, glycerin, glycerol stearate, methyl paraben, petrolatum, polysorbat 80, propyl

paraben, propylene glycol, purified water, sodium citrate, and titanium dioxide.

ACTIVE INGREDIENT (IN EACH GRAM)-HYDROCORTISONE 10 MG

PURPOSE

ANTIPRURITIC (ANTI-ITCH)